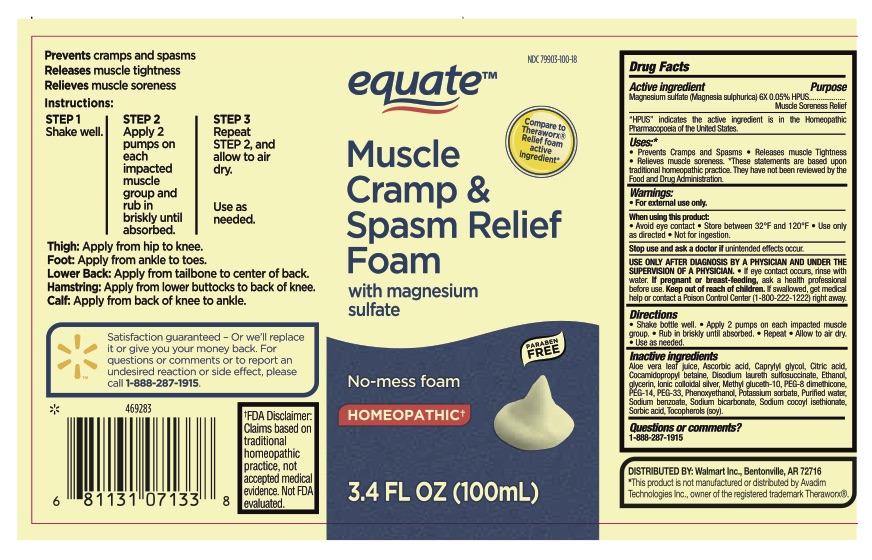 DRUG LABEL: Equate Muscle Cramp and Spasm Relief
NDC: 79903-100 | Form: LIQUID
Manufacturer: Walmart, inc
Category: homeopathic | Type: HUMAN OTC DRUG LABEL
Date: 20251217

ACTIVE INGREDIENTS: MAGNESIUM SULFATE HEPTAHYDRATE 6 [hp_X]/100 mL
INACTIVE INGREDIENTS: WATER; COCAMIDOPROPYL BETAINE; ALOE VERA LEAF; SILVER; GLYCERIN; ASCORBIC ACID; DISODIUM LAURETH SULFOSUCCINATE; SODIUM BENZOATE; SODIUM COCOYL ISETHIONATE; TOCOPHEROL; PEG-8 DIMETHICONE; POTASSIUM SORBATE; ALCOHOL; METHYL GLUCETH-10; POLYETHYLENE GLYCOL 700; PHENOXYETHANOL; CITRIC ACID MONOHYDRATE; POLYETHYLENE GLYCOL 1500; SORBIC ACID; CAPRYLYL GLYCOL; SODIUM BICARBONATE

Equate Muscle Cramp and Spasm Relief Foam

Active Ingredient

Contains Magnesium Sulfate (Magnesia sulphurica) 6X 0.05% HPUS

"HPUS" indicates the active ingredient in this product is in the Homeopathic Pharmacopoeia of the United States.

Purpose

Muscle Soreness Relief

Uses

- Prevents Cramps and Spasms
- Releases Muscle Tightness
- Relieves Muscle Soreness

Warnings

For external use only.

When using this product

- Avoid eye contact
- Store between 32°F and 120°F
- Use only as directed
- Not for ingestion

Stop use

Stop use and ask a doctor if unintended effects occur.

Pregnancy or breast feeding

If pregnant or breastfeeding, ask a health professional before use.

Keep out of reach of children. If swallowed, get medical help or contact a Poison Control Center (1-800-222-1222) right away.

When using

USE ONLY AFTER DIAGNOSIS BY A PHYSICIAN AND UNDER THE SUPERVISION OF A PHYSICIAN. If eye contact occurs, rinse with water.

Directions

Directions • Shake bottle well • Apply 2 pumps on each impacted muscle group. • Rub in briskly until absorbed • Repeat • Allow to air dry • Use as needed

Inactive Ingredients

Aloe vera leaf juice, Ascorbic acid, Caprylyl glycol, Citric acid, Cocamidopropyl betaine, Disodium laureth sulfosuccinate, Ethanol, Glycerin, Ionic colloidal silver, Methyl gluceth-10, PEG-8 Dimethicone, PEG-14, PEG-33, Phenoxyethanol, Potassium sorbate, Purified water, Sodium benzoate, Sodium bicarbonate, Sodium cocoyl isethionate, Sorbic acid, Tocopherols (soy)

Questions...?

Questions or Comments?

1-888-287-1915

Principal Display Panel

FDA Disclaimer: Claims based on traditional homeopathic practice, not accepted medical evidence. Not FDA evaluated.